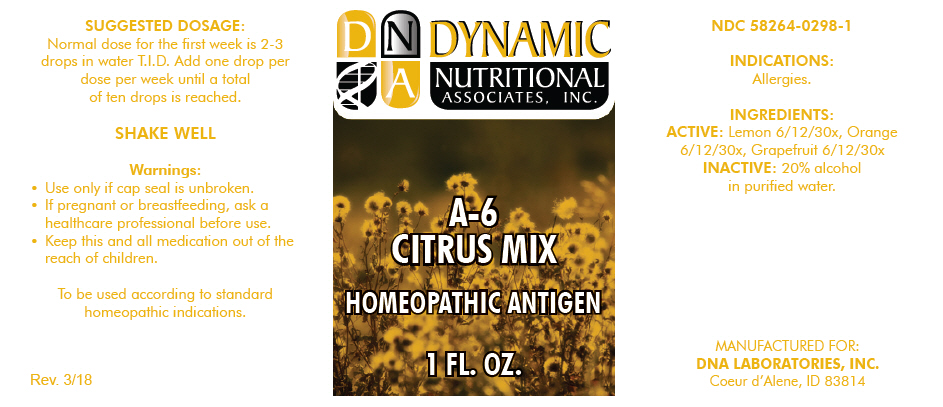 DRUG LABEL: A-6
NDC: 58264-0298 | Form: SOLUTION
Manufacturer: DNA Labs, Inc.
Category: homeopathic | Type: HUMAN OTC DRUG LABEL
Date: 20250109

ACTIVE INGREDIENTS: LEMON 30 [hp_X]/1 mL; ORANGE 30 [hp_X]/1 mL; GRAPEFRUIT 30 [hp_X]/1 mL
INACTIVE INGREDIENTS: ALCOHOL; WATER

A-6

NDC 58264-0298-1

INDICATIONS

PURPOSE

Allergies.

INGREDIENTS

ACTIVE

Lemon 6/12/30x, Orange 6/12/30x, Grapefruit 6/12/30x

INACTIVE

20% alcohol in purified water.

SUGGESTED DOSAGE

Normal dose for the first week is 2-3 drops in water T.I.D. Add one drop per dose per week until a total of ten drops is reached.

STORAGE AND HANDLING

SHAKE WELL

Warnings

- Use only if cap seal is unbroken.

PREGNANCY OR BREAST FEEDING

- If pregnant or breastfeeding, ask a healthcare professional before use.

KEEP OUT OF REACH OF CHILDREN

- Keep this and all medication out of the reach of children.

To be used according to standard homeopathic indications.

PRINCIPAL DISPLAY PANEL - 1 FL. OZ. Bottle Label

DYNAMIC
NUTRITIONAL
ASSOCIATES, INC.

A-6
CITRUS MIX

HOMEOPATHIC ANTIGEN

1 FL. OZ.